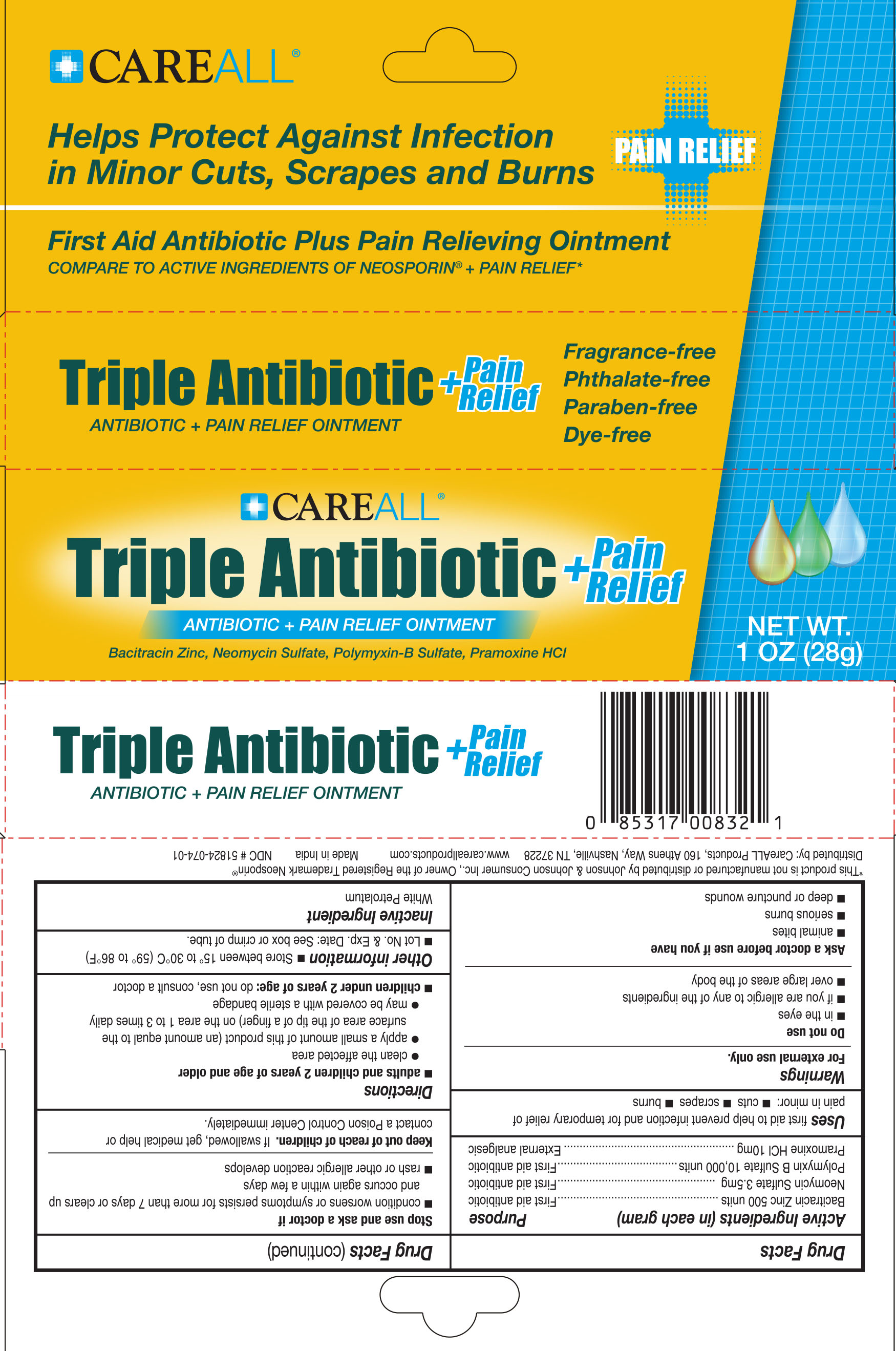 DRUG LABEL: CareALL Triple Antibiotic plus Pain Relief
NDC: 51824-074 | Form: OINTMENT
Manufacturer: New World Imports, Inc
Category: otc | Type: HUMAN OTC DRUG LABEL
Date: 20251201

ACTIVE INGREDIENTS: BACITRACIN ZINC 500 [USP'U]/1 g; NEOMYCIN SULFATE 3.5 mg/1 g; POLYMYXIN B SULFATE 10000 [USP'U]/1 g; PRAMOXINE HYDROCHLORIDE 10 mg/1 g
INACTIVE INGREDIENTS: WHITE PETROLATUM

Active Ingredients (in each gram)

Bacitracin Zinc 500 units

Neomycin Sulfate 3.5 mg

Polymyxin B Sulfate 10,000 units

Pramoxine HCl 10mg

PURPOSE

First aid antibiotic (Bacitracin Zinc 500 units, Neomycin Sulfate 3.5 mg, & Polymyxin B Sulfate 10,000 units)

External Analgesic (Pramoxine HCl 10mg)

Keep out of reach of children. If swallowed, get medical help or contact a poison control center immediately

Uses

First aid to help prevent infection and for temporary relief of pain in minor: cuts, scrapes and burns

Warnings

For external use only

Do not use:

- In the eyes
- If you are allergic to any of the ingredients
- Over large areas of the body

Ask a doctor before use if you have:

- Animal bites
- Serious Burns
- Deep or puncture wounds

Stop use and ask a doctor if:

- Condition worsens or symptoms persists for more than 7 days or clears up and occurs again within a few days
- Rash or other allergic reaction develops

Directions

Adults and children 2 years of age and older:

- Clean the affected area
- Apply a small amount of this product (an amount equal to the surface of the tip of a finger) on the area 1 to 3 times daily
- May be covered with a sterile bandage

Children under 2 years of age: do not use, ask a doctor

Inactive Ingredients

White Petrolatum